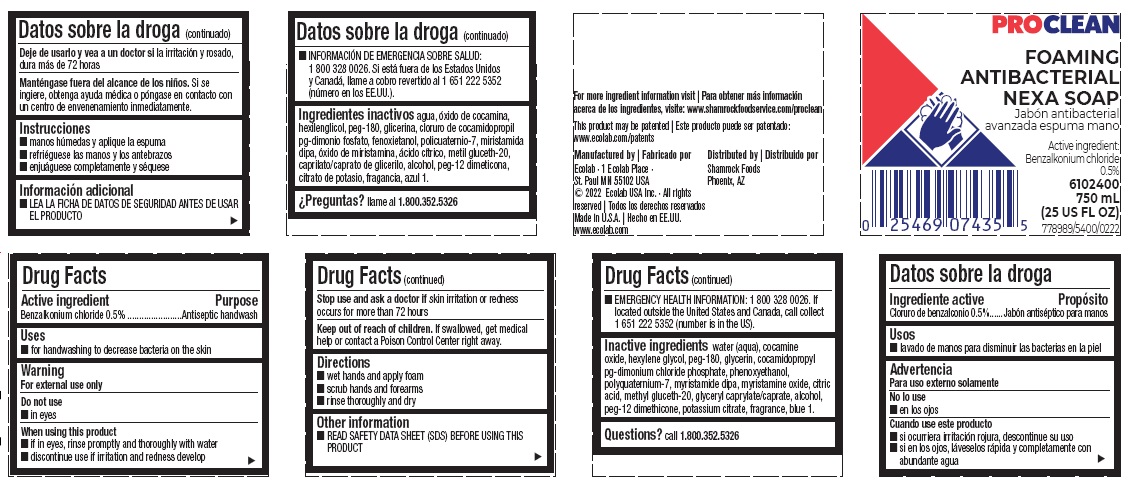 DRUG LABEL: Proclean Foaming Antibacterial Nexa
NDC: 47593-645 | Form: SOLUTION
Manufacturer: Ecolab Inc.
Category: otc | Type: HUMAN OTC DRUG LABEL
Date: 20240806

ACTIVE INGREDIENTS: BENZALKONIUM CHLORIDE 5 mg/1 mL
INACTIVE INGREDIENTS: WATER; COCAMINE OXIDE; HEXYLENE GLYCOL; POLYETHYLENE GLYCOL 8000; GLYCERIN; COCAMIDOPROPYL PG-DIMONIUM CHLORIDE PHOSPHATE; PHENOXYETHANOL; POLYQUATERNIUM-7 (70/30 ACRYLAMIDE/DADMAC; 1600000 MW); MYRISTIC DIISOPROPANOLAMIDE; MYRISTAMINE OXIDE; ANHYDROUS CITRIC ACID; METHYL GLUCETH-20; GLYCERYL MONO- AND DICAPRYLOCAPRATE; ALCOHOL; PEG-12 DIMETHICONE; POTASSIUM CITRATE; FD&C BLUE NO. 1

Drug Facts

Active Ingredient

Benzalkonium chloride 0.5%

Purpose

Antiseptic handwash

Uses

- for handwashing to decrease bacteria on the skin

Warnings

For external use only

Do not use

- in eyes

When using the product

- if in eyes, rinse promptly and thoroughly with water
- discontinue use if irritation and redness develop

Stop use and ask a doctor if skin irritation or redness occurs for more than 72 hours

Keep out of reach of children. If swallowed, get medical help or contact a Poison Control Center right away.

Directions

- wet hands and apply foam
- scrub hands and forearms
- rinse thoroughly and dry

Other information

- READ SAFETY DATA SHEET (SDS) BEFORE USING THIS PRODUCT
- EMERGENCY HEALTH INFORMATIN: 1 800 328 0026. If located outside the United States and Canada, call collect 1 651 222 5352 (number is in the US).

INACTIVE INGREDIENT

Inactive ingredients water (aqua), cocamine oxide, hexylene glycol, PEG-180, glycerin, cocamidopropyl , PG-dimonium chloride phosphate, phenoxyethanol, polyquaternium-7, myristamide DIPA, myristamine oxide, citric acid, methyl gluceth-20, glyceryl caprylate/caprate, alcohol, PEG-12 dimethicone, potassium citrate, fragrance, blue 1

Questions? call 1.800.352.5326

Principal display panel

PROCLEAN
FOAMING ANTIBACTERIAL NEXA SOAP

Active ingredient:
Benzalkonium chloride 0.5%

6102400
750 mL
(25 US FL OZ)

778989/5400/0222

This product may be patented | Este producto puede ser patentado:
www.ecolab.com/patents

Manufactured by | Fabricado por
Ecolab · 1 Ecolab Place ·
St. Paul MN 55102 USA
© 2022 Ecolab USA Inc. · All rights reserved | Todos los derechos reservados
Made in U.S.A. | Hecho en EE.UU.
www.ecolab.com

Distributed by | Distribuido por
Shamrock Foods
Phoenix, AZ